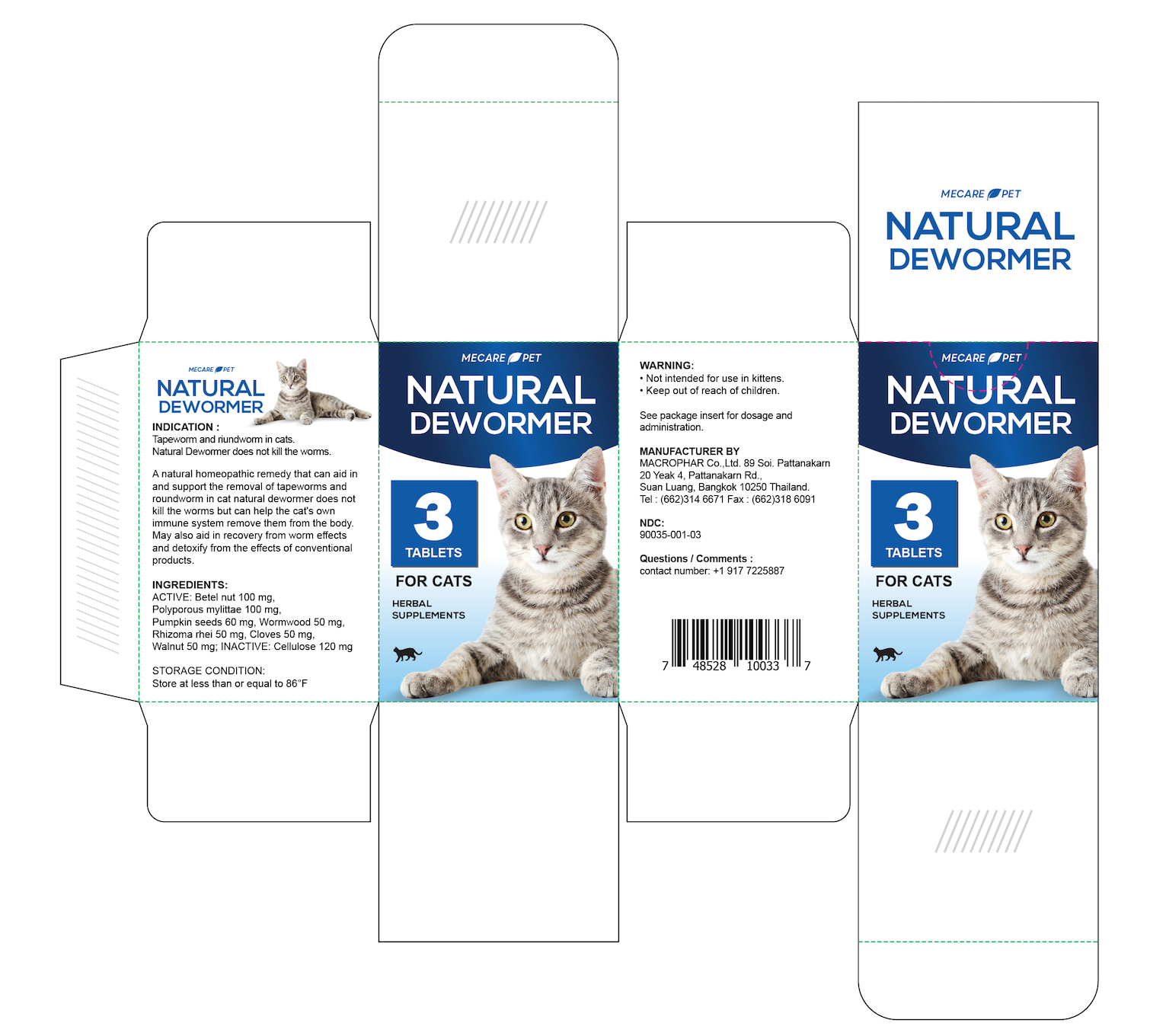 DRUG LABEL: Mecare Pet Natural Dewormer Cats
NDC: 90035-001 | Form: TABLET
Manufacturer: MacroPhar Co.,Ltd.
Category: homeopathic | Type: OTC ANIMAL DRUG LABEL
Date: 20210212

ACTIVE INGREDIENTS: LACCOCEPHALUM MYLITTAE WHOLE 100 mg/1 1; ARECA CATECHU FRUIT RIND 100 mg/1 1; ENGLISH WALNUT 50 mg/1 1; WORMWOOD 50 mg/1 1; ALISMA PLANTAGO-AQUATICA SUBSP. ORIENTALE ROOT 50 mg/1 1; CLOVE 50 mg/1 1; PUMPKIN SEED 60 mg/1 1
INACTIVE INGREDIENTS: POWDERED CELLULOSE 120 mg/1 1

Mecare Pet Natural Dewormer Cats

Indications

For the treatment of gastrointestinal tapeworm and roundworm in cats.

Natural Dewormer is a natural homeopathic remedy that can aid in and support the removal of tapeworm and roundworm in cats. Natural Dewormer does not kill the worms but can help the cat's own immune system remove them from the body. May also aid in recovery from worm effects and detoxify from the effects of conventional products.

Active Ingredients

Betel nut 100 mg, Polyporous mylittae 100 mg, Pumpkin seeds 60 mg, Wormwood 50 mg, Rhizoma rhei 50 mg, Cloves 50 mg, Walnut 50 mg

Inactive Ingredients

Cellulose 120 mg

Storage Condition

Store at less than or equal to 30°C (86°F)

Warning

Not intended for use in kittens less than 6 weeks of age.

KEEP OUT OF REACH OF CHILDREN.

Dosage and Administration

PLEASE SEE PACKAGE INSERT FOR COMPLETE DIRECTIONS FOR USE.

OTHER SAFETY INFORMATION

MANUFACTURER BY

MACROPHAR Co.,Ltd. 89 Soi. Pattanakarn
20 Yeak 4, Pattanakarn Rd.,

Suan Luang, Bangkok 10250 Thailand.
Tel : (662)314 6671 Fax : (662)318 6091

NDC:

90035-001-03

Questions and Comments

Contact number: +1 917 7225887

Package Insert

When using this product:

Do not use simultaneously with piperazine compounds.
Do not use during pregnancy.

Dosage and Administration:

The coated tablets should be given directly, but if necessary can be disguised in food. Adult cats: Single oral administration every 3 months or according to veterinary advice. Kittens: Single oral administration at 6, 8, 10, and 12 weeks and then monthly until 6 months of age. Afterward, every 3 months or according to veterinary advice.

Dosage

Bodyweight ≥4.4 lbs: 1/2 tablets

Bodyweight ≥8.8 lbs: 1 tablet

Bodyweight ≥13.0 lbs: 1 1/2 tablets

Principal Display Panel

Natural Dewormer Cats, 3 tablets NDC: 90035-001-03